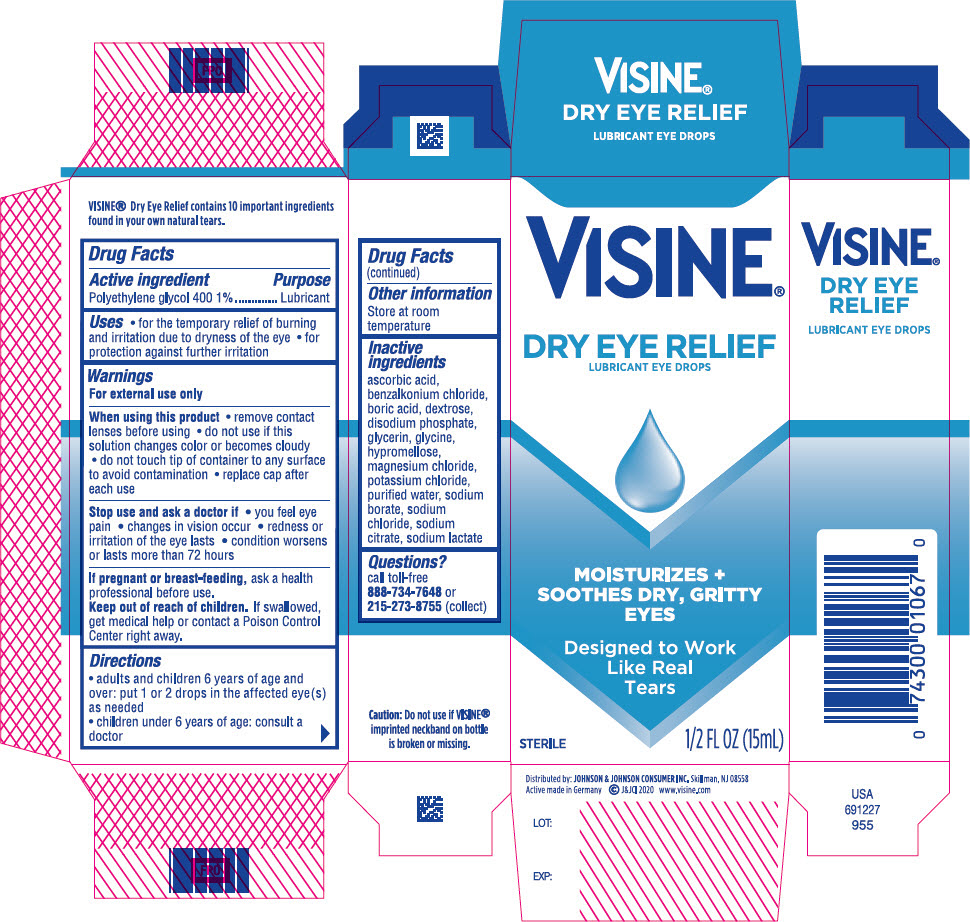 DRUG LABEL: Visine Dry Eye Relief
NDC: 69968-0363 | Form: SOLUTION/ DROPS
Manufacturer: Kenvue Brands LLC
Category: otc | Type: HUMAN OTC DRUG LABEL
Date: 20241113

ACTIVE INGREDIENTS: POLYETHYLENE GLYCOL 400 10 mg/1 mL
INACTIVE INGREDIENTS: ASCORBIC ACID; BENZALKONIUM CHLORIDE; BORIC ACID; DEXTROSE, UNSPECIFIED FORM; SODIUM PHOSPHATE, DIBASIC, ANHYDROUS; GLYCERIN; GLYCINE; HYPROMELLOSE, UNSPECIFIED; MAGNESIUM CHLORIDE; POTASSIUM CHLORIDE; WATER; SODIUM BORATE; SODIUM CHLORIDE; SODIUM CITRATE, UNSPECIFIED FORM; SODIUM LACTATE

VISINE® Dry Eye Relief

Drug Facts

Active ingredient

Polyethylene glycol 400 1%

Purpose

Lubricant

Uses

- for the temporary relief of burning and irritation due to dryness of the eye
- for protection against further irritation

Warnings

For external use only

When using this product

- remove contact lenses before using
- do not use if this solution changes color or becomes cloudy
- do not touch tip of container to any surface to avoid contamination
- replace cap after each use

Stop use and ask a doctor if

- you feel eye pain
- changes in vision occur
- redness or irritation of the eye lasts
- condition worsens or lasts more than 72 hours

PREGNANCY OR BREAST FEEDING

If pregnant or breast-feeding, ask a health professional before use.

Keep out of reach of children. If swallowed, get medical help or contact a Poison Control Center right away.

Directions

- adults and children 6 years of age and over: put 1 or 2 drops in the affected eye(s) as needed
- children under 6 years of age: consult a doctor

Other information

Store at room temperature

Inactive ingredients

ascorbic acid, benzalkonium chloride, boric acid, dextrose, disodium phosphate, glycerin, glycine, hypromellose, magnesium chloride, potassium chloride, purified water, sodium borate, sodium chloride, sodium citrate, sodium lactate

Questions?

call toll-free 888-734-7648 or 215-273-8755 (collect)

Distributed by: JOHNSON & JOHNSON CONSUMER INC. Skillman, NJ 08558

PRINCIPAL DISPLAY PANEL - 15 mL Bottle Carton

VISINE®

DRY EYE RELIEF

LUBRICANT EYE DROPS

MOISTURIZES +

SOOTHES DRY, GRITTY

EYES

Designed to work

Like Real

Tears

STERILE

1/2 FL OZ (15 mL)